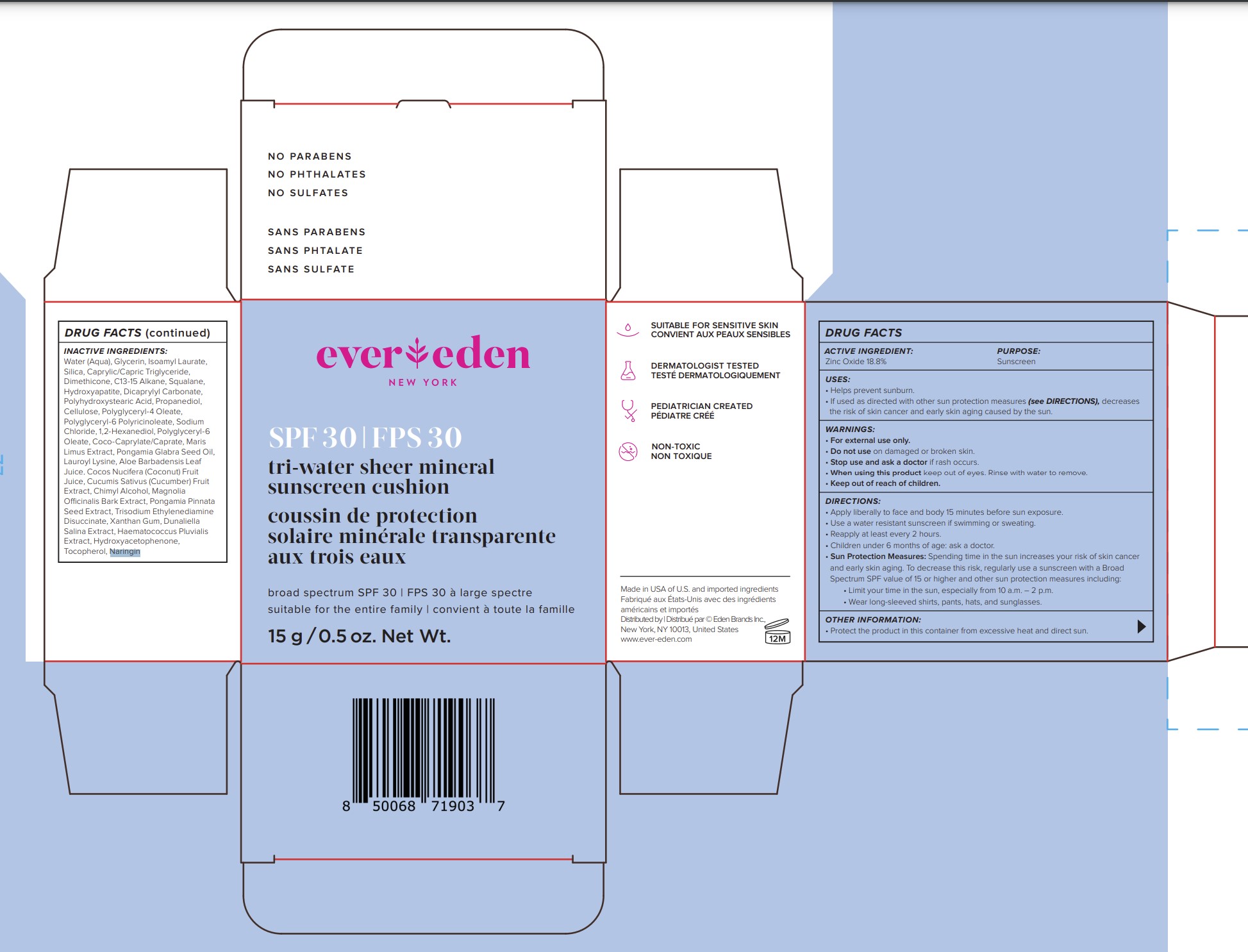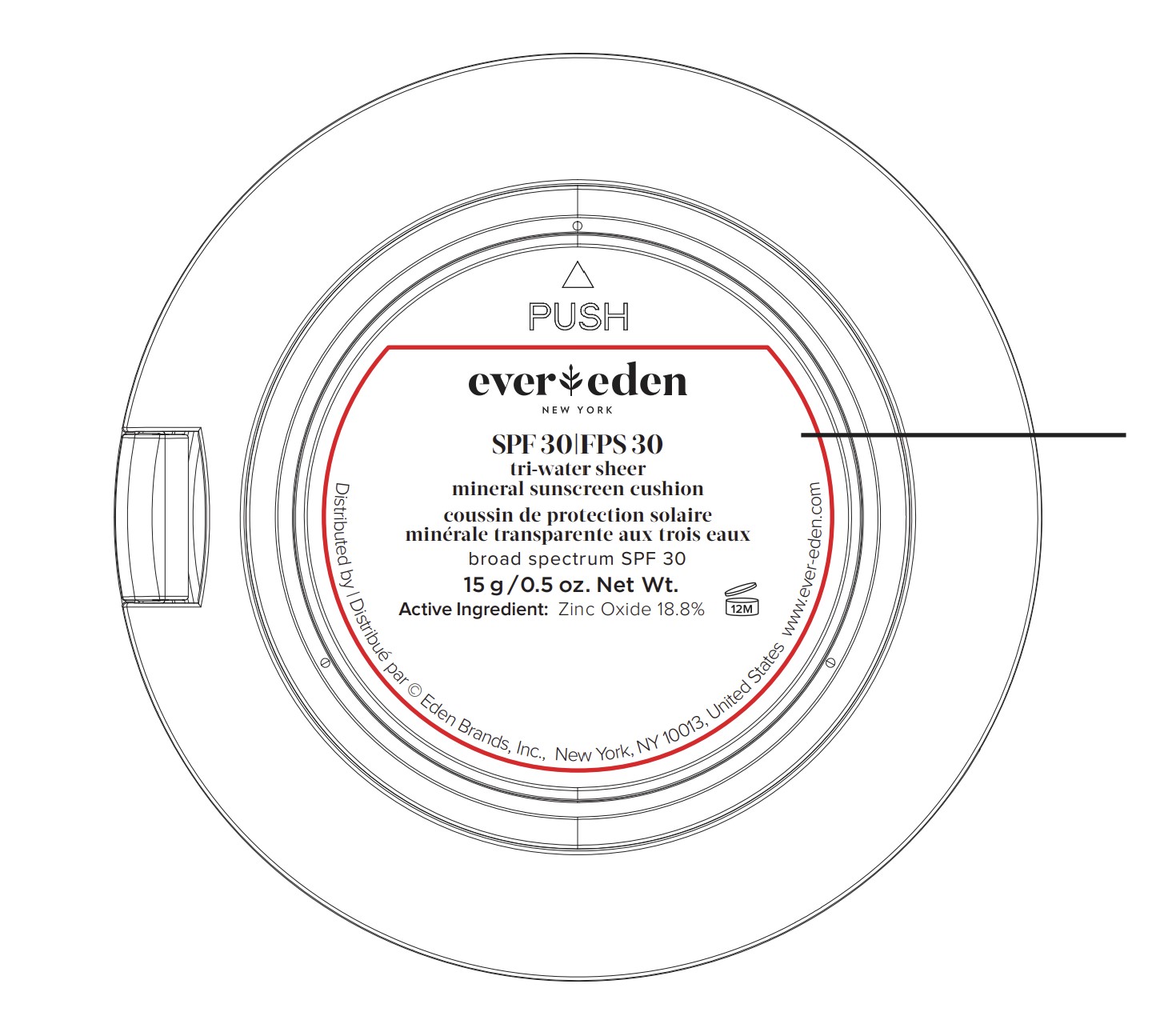 DRUG LABEL: Tri-water sheer mineral sunscreen cushion SPF30
NDC: 72113-111 | Form: SPONGE
Manufacturer: Eden Brands Inc.
Category: otc | Type: HUMAN OTC DRUG LABEL
Date: 20250128

ACTIVE INGREDIENTS: ZINC OXIDE 188 mg/1 g
INACTIVE INGREDIENTS: C13-15 ALKANE; PROPANEDIOL; POWDERED CELLULOSE; POLYGLYCERYL-4 OLEATE; 1,2-HEXANEDIOL; COCO-CAPRYLATE/CAPRATE; MAGNOLIA OFFICINALIS BARK; TRISODIUM ETHYLENEDIAMINE DISUCCINATE; TOCOPHEROL; GLYCERIN; POLYGLYCERYL-6 POLYRICINOLEATE; POLYGLYCERYL-6 OLEATE; COCONUT JUICE; PONGAMIA PINNATA SEED; HYDROXYAPATITE; CHIMYL ALCOHOL; DICAPRYLYL CARBONATE; POLYHYDROXYSTEARIC ACID (2300 MW); ISOAMYL LAURATE; CAPRYLIC/CAPRIC TRIGLYCERIDE; DIMETHICONE, UNSPECIFIED; SQUALANE; SILICON DIOXIDE; KARUM SEED OIL; HYDROXYACETOPHENONE; ALOE VERA LEAF; CUCUMBER; HAEMATOCOCCUS PLUVIALIS; NARINGIN; LAUROYL LYSINE; WATER; XANTHAN GUM; DUNALIELLA SALINA; SODIUM CHLORIDE

ACTIVE INGREDIENT:

Zinc Oxide 18.8%

PURPOSE:

Sunscreen

USES:

• Helps prevent sunburn.

• If used as directed with other sun protection measures (see DIRECTIONS), decreases the risk of skin cancer and early skin aging caused by the sun.

WARNINGS:

• For external use only

• Do not use on damaged or broken skin.

• Stop use and ask a doctor if rash occurs.

• When using this product keep out of eyes. Rinse with water to remove.

Keep out of reach of children.

DIRECTIONS:

• Apply liberally to face and body 15 minutes before sun exposure.

• Use a water resistant sunscreen if swimming or sweating.

• Reapply at least every 2 hours.

• Children under 6 months of age: ask a doctor.

• Sun Protection Measures: Spending time in the sun increases your risk of skin cancer and early skin aging. To decrease this risk, regularly use a sunscreen with a Broad Spectrum SPF value of 15 or higher and other sun protection measures including:

• Limit your time in the sun, especially from 10 a.m. – 2 p.m.

• Wear long-sleeved shirts, pants, hats, and sunglasses.

OTHER INFORMATION:

• Protect the product in this container from excessive heat and direct sun.

INACTIVE INGREDIENTS:

Water (Aqua), Glycerin, Isoamyl Laurate, Silica, Caprylic/Capric Triglyceride, Dimethicone, C13-15 Alkane, Squalane, Hydroxyapatite, Dicaprylyl Carbonate, Polyhydroxystearic Acid, Propanediol, Cellulose, Polyglyceryl-4 Oleate, Polyglyceryl-6 Polyricinoleate, Sodium Chloride, 1,2-Hexanediol, Polyglyceryl-6 Oleate, Coco-Caprylate/Caprate, Maris Limus Extract, Pongamia Glabra Seed Oil, Lauroyl Lysine, Aloe Barbadensis Leaf Juice, Cocos Nucifera (Coconut) Fruit Juice, Cucumis Sativus (Cucumber) Fruit Extract, Chimyl Alcohol, Magnolia Officinalis Bark Extract, Pongamia Pinnata Seed Extract, Trisodium Ethylenediamine Disuccinate, Xanthan Gum, Dunaliella Salina Extract, Haematococcus Pluvialis Extract, Hydroxyacetophenone, Tocopherol, Naringin